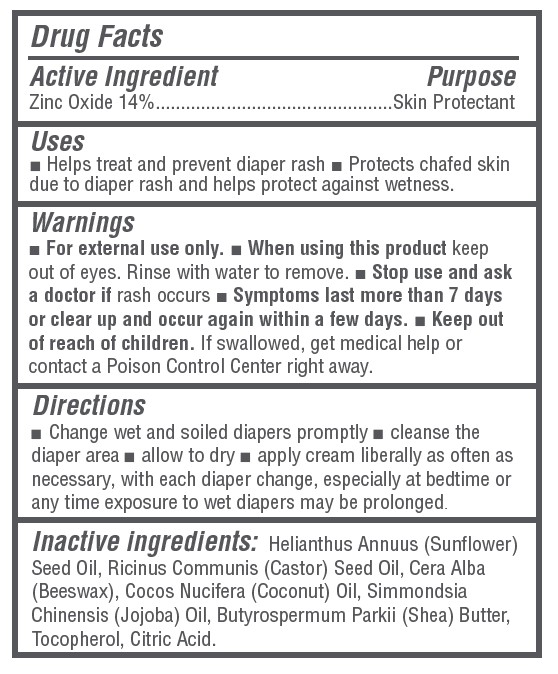 DRUG LABEL: Baby Diaper Rash Cream
NDC: 73418-301 | Form: CREAM
Manufacturer: Hello Bello
Category: otc | Type: HUMAN OTC DRUG LABEL
Date: 20251106

ACTIVE INGREDIENTS: ZINC OXIDE 400 mg/1 g
INACTIVE INGREDIENTS: CITRIC ACID; BEESWAX; JOJOBA OIL; SUNFLOWER OIL; CASTOR OIL; SHEA BUTTER; TOCOPHEROL; COCONUT OIL

Baby Diaper Rash Cream

Drug Facts

Active Ingredients

Zinc Oxide - 40%

Purpose

Skin Protectant

Uses

- Helps treat and prevent diaper rash
- Protects chafed skin due to diaper rash and helps seal out wetness

Warnings

For external use only

When using this product,

do not get into eyes

Stop use and ask a doctor

if condition worsens or symptoms last more than 7 days or clear up and occur again within a few days

Keep out of reach of children

If swallowed, get medical help or contact a Poison Control Center right away

Directions

- Change wet and soiled diapers promptly.
- Cleanse the diaper area and allow to dry.
- Apply cream liberally as often as necessary, with each diaper change, and especially at bedtime or anytime when exposure to wet diapers may be prolonged

Other Information

- Do not use if quality seal is broken
- Do not store above 40C (104F)

Inactive Ingredients

Sunflower Seed Oil, Castor Seed Oil, Cera Alba (Beeswax), Cocos Nucifera Oil, Simmondsia Chinensis (Jojoba) Oil, Shea Butter, Tocopherol, Citric Acid